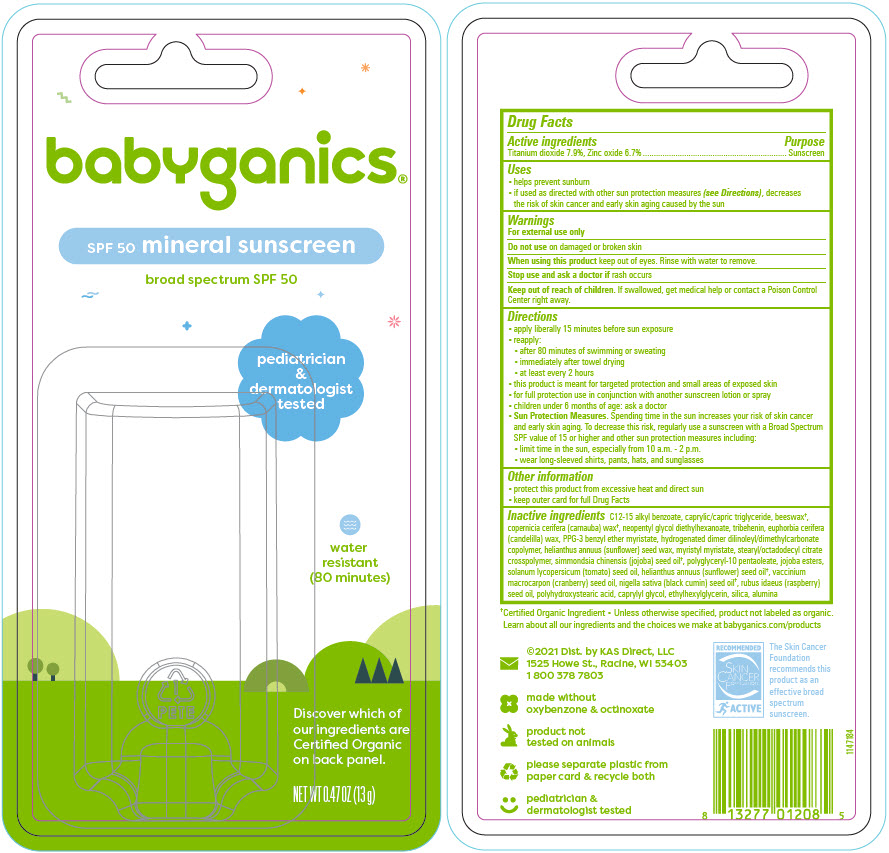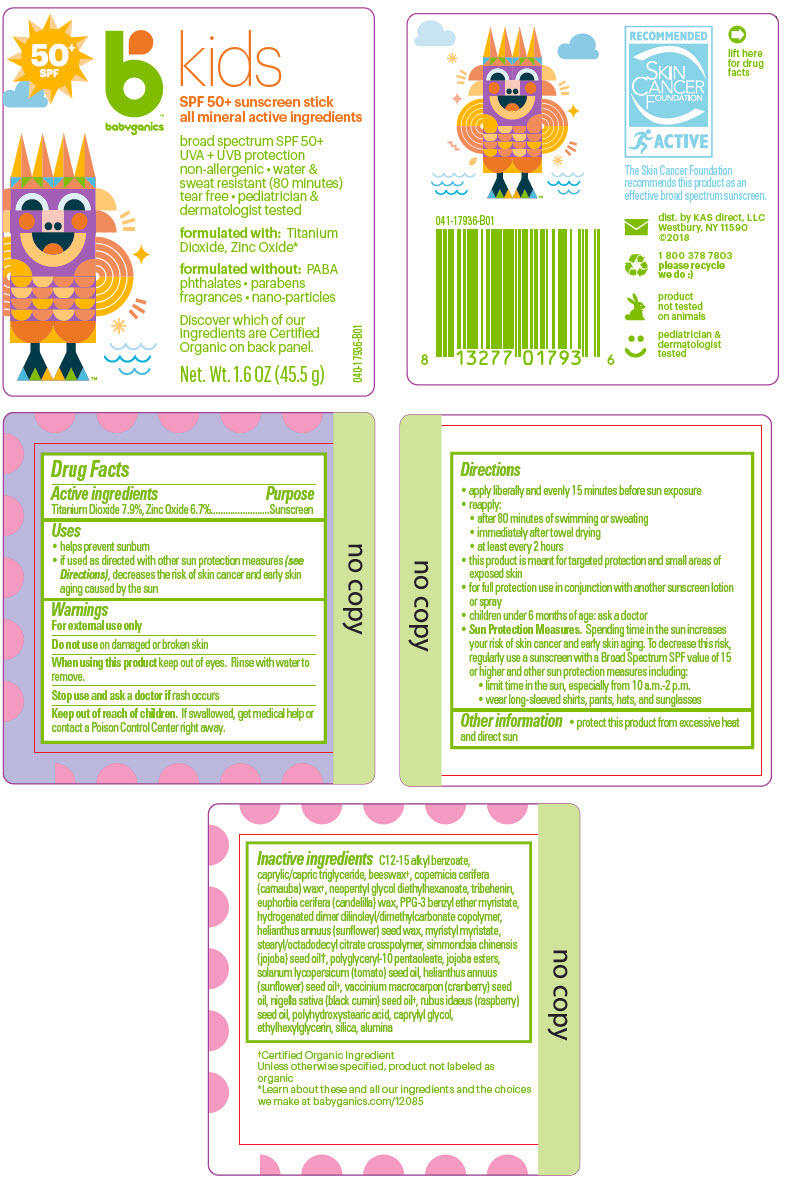 DRUG LABEL: SPF 50 plus Sunscreen 
NDC: 59062-1200 | Form: STICK
Manufacturer: KAS Direct LLC dba BabyGanics
Category: otc | Type: HUMAN OTC DRUG LABEL
Date: 20241218

ACTIVE INGREDIENTS: TITANIUM DIOXIDE 79 mg/1 g; ZINC OXIDE 67 mg/1 g
INACTIVE INGREDIENTS: ALKYL (C12-15) BENZOATE; YELLOW WAX; CARNAUBA WAX; MEDIUM-CHAIN TRIGLYCERIDES; NEOPENTYL GLYCOL DIETHYLHEXANOATE; TRIBEHENIN; CANDELILLA WAX; PPG-3 BENZYL ETHER MYRISTATE; MYRISTYL MYRISTATE; HELIANTHUS ANNUUS SEED WAX; Stearyl/Octyldodecyl Citrate Crosspolymer; JOJOBA OIL; Polyglyceryl-10 Pentaoleate; CAPRYLYL GLYCOL; ETHYLHEXYLGLYCERIN; JOJOBA OIL, RANDOMIZED; RASPBERRY SEED OIL; CRANBERRY SEED OIL; SUNFLOWER OIL; TOMATO SEED OIL; NIGELLA SATIVA SEED OIL; POLYHYDROXYSTEARIC ACID (2300 MW); Silicon Dioxide; Aluminum Oxide

SPF 50+ Sunscreen Stick
All Mineral Active Ingredients

Drug Facts

Active ingredients

Titanium Dioxide 7.9%, Zinc Oxide 6.7%

Purpose

Sunscreen

Uses

- helps prevent sunburn
- if used as directed with other sun protection measures (see Directions), decreases the risk of skin cancer and early skin aging caused by the sun

Warnings

For external use only

Do not use on damaged or broken skin

When using this product keep out of eyes. Rinse with water to remove.

Stop use and ask a doctor if rash occurs

Keep out of reach of children. If swallowed, get medical help or contact a Poison Control Center right away.

Directions

- apply liberally and evenly 15 minutes before sun exposure
- reapply:
  - after 80 minutes of swimming or sweating
  - immediately after towel drying
  - at least every 2 hours
- this product is meant for targeted protection and small areas of exposed skin
- for full protection use in conjunction with another sunscreen lotion or spray
- children under 6 months of age: ask a doctor
- Sun Protection Measures. Spending time in the sun increases your risk of skin cancer and early skin aging. To decrease this risk, regularly use a sunscreen with a Broad Spectrum SPF value of 15 or higher and other sun protection measures including:
  - limit time in the sun, especially from 10 a.m.-2 p.m.
  - wear long-sleeved shirts, pants, hats, and sunglasses

Other information

- protect this product from excessive heat and direct sun
- keep outer card for full drug facts

Inactive ingredients

C12-15 alkyl benzoate, caprylic/capric triglyceride, beeswax [Certified Organic Ingredient • Unless otherwise specified, product not labeled as organic] , copernicia cerifera (carnauba) wax, neopentyl glycol diethylhexanoate, tribehenin, euphorbia cerifera (candelilla) wax, PPG-3 benzyl ether myristate, hydrogenated dimer dilinoleyl/dimethylcarbonate copolymer, helianthus annuus (sunflower) seed wax, myristyl myristate, stearyl/octadodecyl citrate crosspolymer, simmondsia chinensis (jojoba) seed oil, polyglyceryl-10 pentaoleate, jojoba esters, solanum lycopersicum (tomato) seed oil, helianthus annuus (sunflower) seed oil, vaccinium macrocarpon (cranberry) seed oil, nigella sativa (black cumin) seed oil, rubus idaeus (raspberry) seed oil, polyhydroxystearic acid, caprylyl glycol, ethylhexylglycerin, silica, alumina

dist. by KAS direct, LLC
Westbury, NY 11590

PRINCIPAL DISPLAY PANEL - 13 g Applicator Blister Pack

babyganics®

SPF 50 mineral sunscreen

broad spectrum SPF 50

pediatrician
&
dermatologist
tested

water
resistant
(80 minutes)

Discover which of
our ingredients are
Certified Organic
on back panel.

NET WT 0.47 OZ (13 g)

PRINCIPAL DISPLAY PANEL - 45.5 g Applicator Label

50^+
SPF

babyganics

kids

SPF 50+ sunscreen stick
all mineral active ingredients

broad spectrum SPF 50+
UVA + UVB protection
non-allergenic • water &
sweat resistant (80 minutes)
tear free • pediatrician &
dermatologist tested

formulated with: Titanium
Dioxide, Zinc Oxide*

formulated without: PABA
phthalates • parabens
fragrances • nano-particles

Discover which of our
ingredients are Certified
Organic on back panel.

Net. Wt. 1.6 OZ (45.5 g)

040-17936-B01